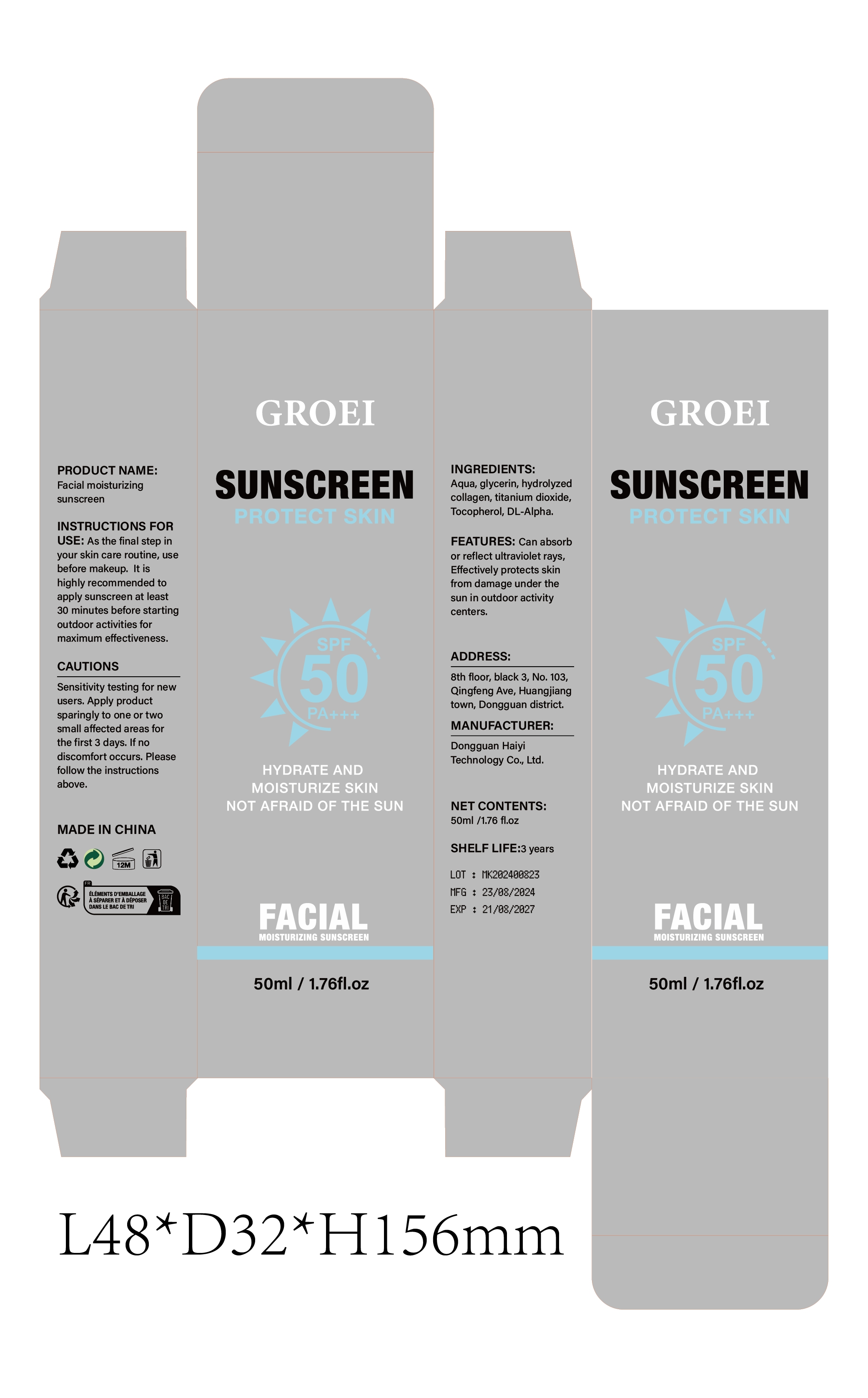 DRUG LABEL: Facial moisturizing sunscreen
NDC: 84732-032 | Form: CREAM
Manufacturer: Dongguan Haiyi Technology Co.,Ltd.
Category: otc | Type: HUMAN OTC DRUG LABEL
Date: 20241008

ACTIVE INGREDIENTS: EQUINE COLLAGEN 1 mg/50 mL
INACTIVE INGREDIENTS: WATER; TOCOPHEROL; GLYCERIN; TITANIUM DIOXIDE; .ALPHA.-TOCOPHEROL ACETATE, DL-

Active ingredient

Hydrolyzed Collagen

Inactive ingredient

Aqua, glycerin, titanium dioxide,Tocopherol, DL-Alpha.

Purpose section

Can absorbor reflect ultraviolet rays,Effectively protects skinfrom damage under thesun in outdoor activitycenters.

Warning

Sensitivity testing for newusers. Apply productsparingly to one or twosmall affected areas forthe first 3 days. lf nodiscomfort occurs. Pleasefollow the instructionsabove.

stop use

This product may cause allergic reactions in asmall number of people.
lf youexperience any discomfort,please stop using it immediately.

not use

Not suitable for use by children, pregnantor breast feeding people.

OUT OF CHILDREN

KEEP THE PRODUCT OUT OF REACH OF CHILDREN to

HOW TO USE

As the final step inyour skin care routine, usebefore makeup. lt ishighly recommended toapply sunscreen at least30 minutes before startingoutdoor activities formaximum effectiveness.

Dosage

It is recommended to use enough sunscreen to cover the entire surface of skin exposed to the sun and reapply every 2 hours after each use, especially after swimming, sweating or wiping the skin.